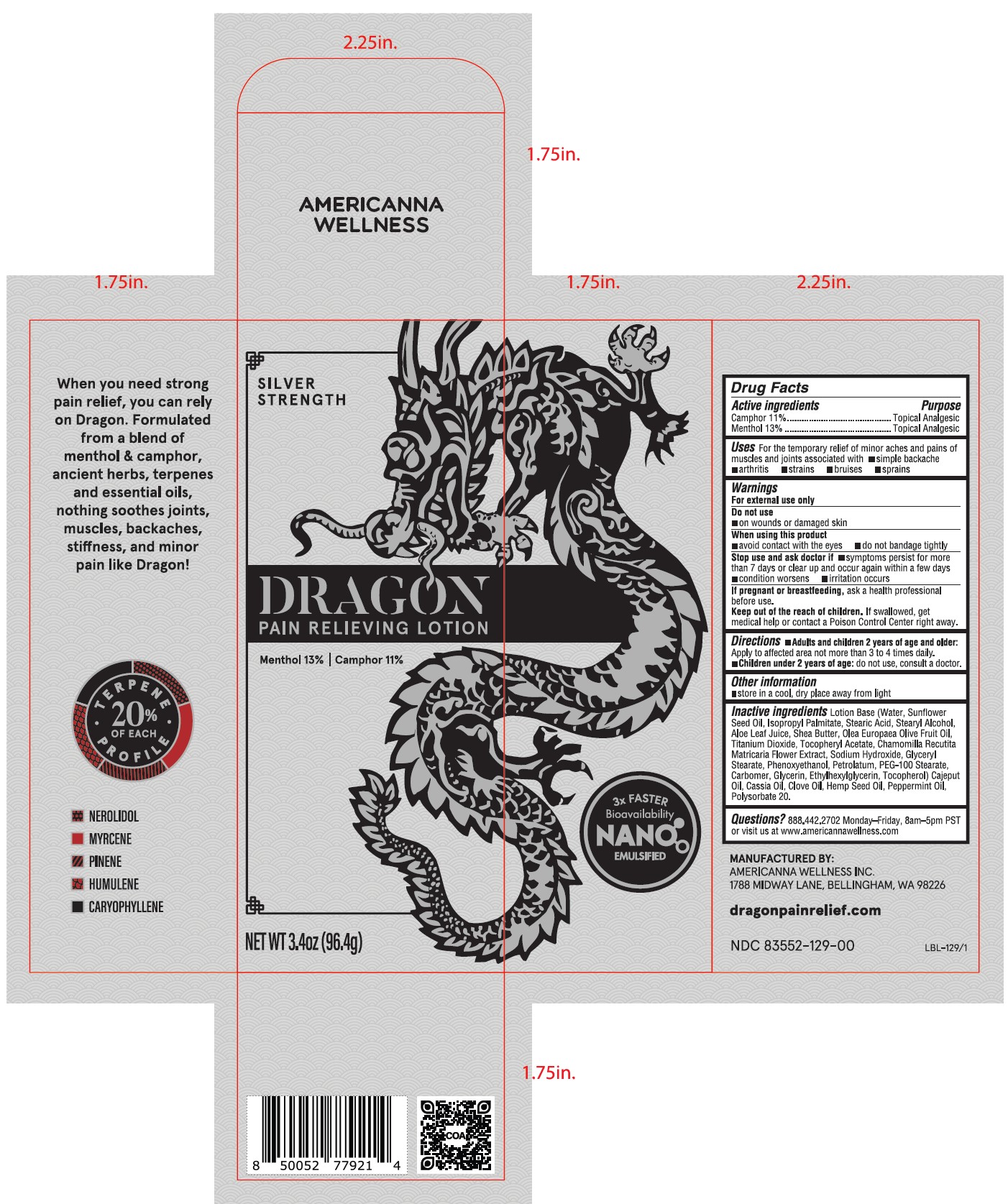 DRUG LABEL: Dragon Pain Relieving
NDC: 83552-129 | Form: LOTION
Manufacturer: Americanna Wellness, Inc.
Category: otc | Type: HUMAN OTC DRUG LABEL
Date: 20240410

ACTIVE INGREDIENTS: CAMPHOR (NATURAL) 11 g/100 g; MENTHOL 13 g/100 g
INACTIVE INGREDIENTS: PHENOXYETHANOL; SUNFLOWER OIL; CARBOMER HOMOPOLYMER, UNSPECIFIED TYPE; STEARYL ALCOHOL; SHEA BUTTER; TITANIUM DIOXIDE; SODIUM HYDROXIDE; PEG-100 STEARATE; GLYCERIN; ETHYLHEXYLGLYCERIN; STEARIC ACID; ALOE; POLYSORBATE 20; WATER; TOCOPHEROL; ISOPROPYL PALMITATE; .ALPHA.-TOCOPHEROL ACETATE; GLYCERYL MONOSTEARATE; PETROLATUM; CAJUPUT OIL; CANNABIS SATIVA SEED OIL; CLOVE OIL; PEPPERMINT OIL; CHINESE CINNAMON OIL; OLIVE OIL; CHAMOMILE

Active ingredients

Camphor 11%

Menthol 13%

Purpose

Camphor 11%.....................Topical Analgesic

Menthol 13%.......................Topical Analgesic

Uses

For the temporary relief of minor achse and pains of muscles and joints associated with

- simple backache
- arthritis
- strains
- bruises
- sprains

Warnings

For external use only

Do not use

- on wounds or damaged skin

When using this product

- avoid contact with the eyes
- do not bandage tightly

Stop use and ask doctor if

- symptoms persist for more than 7 days or clear up and occur again within a few days
- condition worsens
- irritation occurs

PREGNANCY OR BREAST FEEDING

If pregnant or breastfeeding, ask a health professional before use.

Keep out of reach of children. If swallowed, get medical help or contact a Poison Control Center right away.

Directions

- Adults and children 2 years of age and older: Apply to affected area not more than 3 to 4 times daily.
- Children under 2 years of age: do not use, consult a doctor.

Other information

- store in a cool, dry place away from light

Inactive ingredients

Lotion Base (Water, Sunflower Seed Oil, Isopropyl Palmitate, Stearic Acid, Stearyl Alcohol, Aloe Leaf Juice, Shea Butter, Olea Europaea Olive Fruit Oil, Titanium Dioxide, Tocopheryl Acetate, Chamomilla REcutita Matricaria Flower Extract, Sodium Hydroxide, Glyceryl Stearate, Phenoxyethanol, Petrolatum, PEG-100 Stearate, Carbomer, Glycerin, Ethylhexylglycerin, Tocopherol) Cajeput Oil, Cassia Oil, Clove Oil, Hemp Seed Oil, Peppermint Oil, Polysorbate 20.

Questions?

888.442.2702 Monday-Friday, 8am-5pm PST or visit us at www.americannawellness.com

PACKAGE LABEL

Silver Strength

Dragon Pain Relieving Lotion

Menthol 13% | Camphor 11%

Net Wt 3.4oz (96.4g)